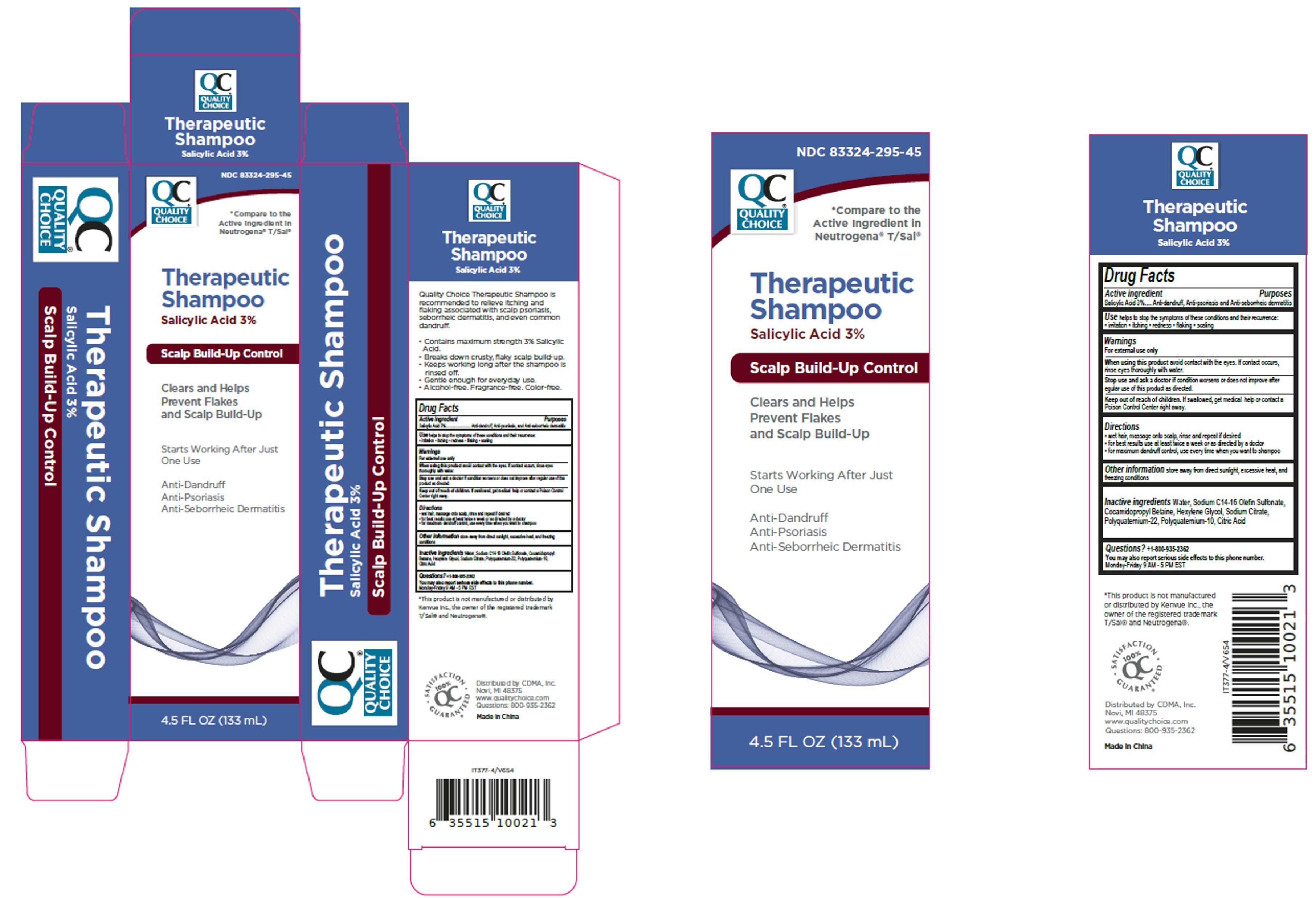 DRUG LABEL: Quality Choice Therapeutic
NDC: 83324-295 | Form: SHAMPOO
Manufacturer: Chain Drug Marketing Association, Inc.
Category: otc | Type: HUMAN OTC DRUG LABEL
Date: 20251223

ACTIVE INGREDIENTS: SALICYLIC ACID 3 g/100 mL
INACTIVE INGREDIENTS: SODIUM CITRATE; POLYQUATERNIUM-10 (1000 MPA.S AT 2%); POLYQUATERNIUM-22 (4500 MPA.S); CITRIC ACID; WATER; SODIUM C14-16 OLEFIN SULFONATE; COCAMIDOPROPYL BETAINE; HEXYLENE GLYCOL

QC Thera - Longway

Active Ingredient

Salicylic Acid 3%

Purpose

Anti-dandruff, Anti-psoriasis, and Anti-seborrheic dermatitis

Uses

helps to stop the symptoms of these conditions and their recurrence: ▪ irritation ▪ itching ▪ redness ▪ flaking ▪ scaling

Warnings For external use only

When using this product

avoid contact with the eyes. If contact occurs, rinse eyes thoroughly with water.

Stop use and ask doctor if

condition worsens or does not improve after regular use of this product as directed.

KEEP OUT OF REACH OF CHILDREN

Keep out of the reach of children. If swallowed, get medical help or contact a Poison Control Center right away.

Directions

▪ wet hair, massage onto scalp, rinse and repeat if desired
▪ for best results use at least twice a week or as directed by a doctor
▪ for maximum dandruff control, use every time when you want to shampoo

Other information

store away from direct sunlight, excessive heat, and freezing conditions

Inactive ingredients

Water, Sodium C14-16 Olefin Sulfonate, Cocamidopropyl
Betaine, Hexylene Glycol, Sodium Citrate, Polyquaternium-22, Polyquaternium-10,
Citric Acid

Questions? +1-800-935-2362
You may also report serious side effects to this phone number.
Monday-Friday 9 AM - 5 PM EST